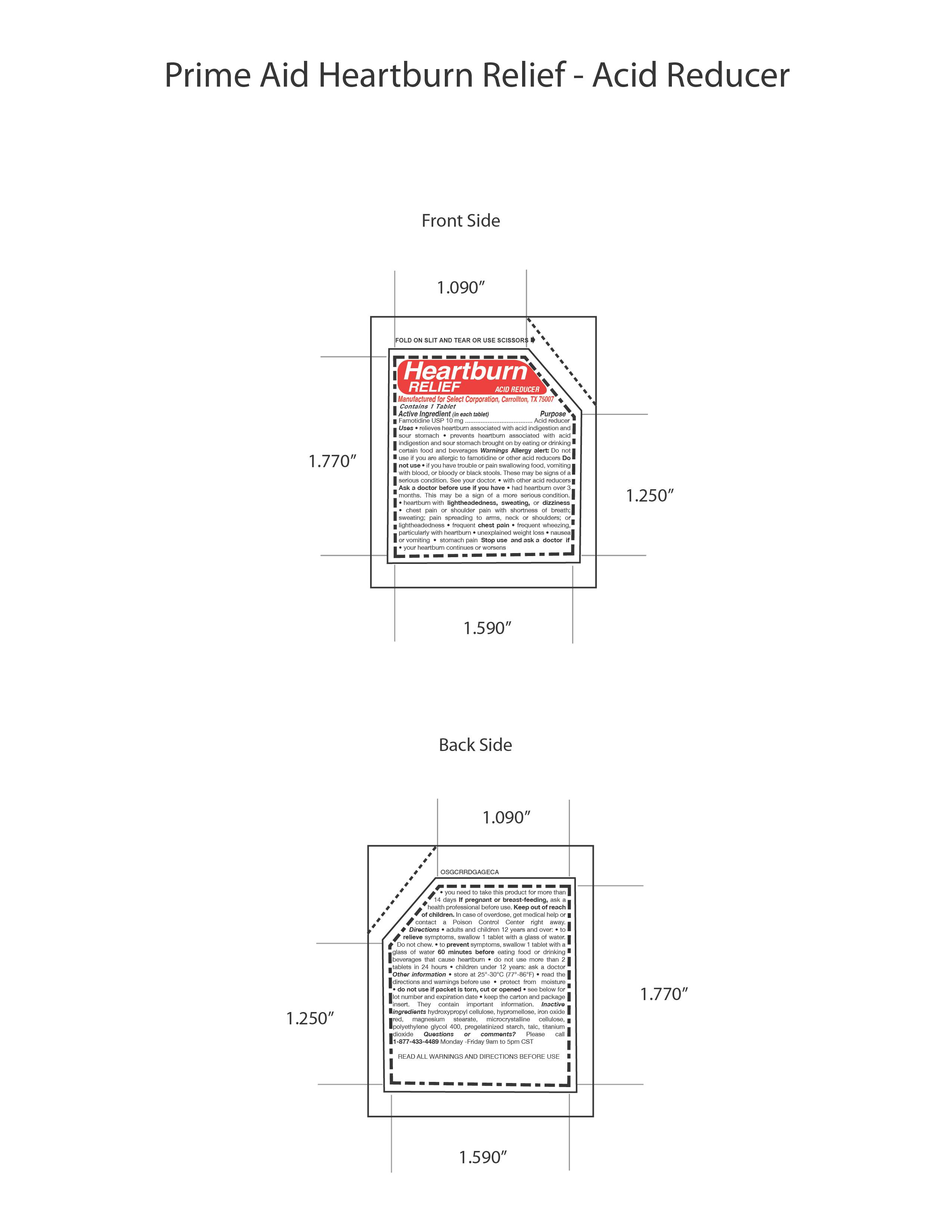 DRUG LABEL: Heartburn Relief 
NDC: 52904-448 | Form: TABLET
Manufacturer: Select Corporation
Category: otc | Type: HUMAN OTC DRUG LABEL
Date: 20140414

ACTIVE INGREDIENTS: FAMOTIDINE 10 mg/1 1
INACTIVE INGREDIENTS: TALC; STARCH, CORN; POLYETHYLENE GLYCOL 400; CELLULOSE, MICROCRYSTALLINE; MAGNESIUM STEARATE; TITANIUM DIOXIDE; FERRIC OXIDE RED

Drug Facts

Active Ingredients

Famotidine USP 10mg

PURPOSE

Acid Reducer

DOSAGE AND ADMINISTRATION

Directions • adults and

children 12 years and over: • to relieve symptoms,

swallow 1 tablet with a glass of water. Do not chew.

• to prevent symptoms, swallow 1 tablet with a

glass of water 60 minutes before eating food or

drinking beverages that cause heartburn • do not

use more than 2 tablets in 24 hours • children under

12 years: ask a doctor

INDICATIONS AND USAGE

Uses: • relieves heartburn associated with acid

indigestion and sour stomach • prevents heartburn

associated with acid indigestion and sour stomach

brought on by eating or drinking certain food and

beverages

Warnings: Allergy alert: Do not use if

you are allergic to famotidine or other acid reducers

Do not use • if you have trouble or pain swallowing

food, vomiting with blood, or bloody or black stools.

These may be signs of a serious condition. See your

doctor. • with other acid reducers Ask a doctor

before use if you have • had heartburn over 3

months. This may be a sign of a more serious

condition. • heartburn with lightheadedness,

sweating, or dizziness • chest pain or shoulder

pain with shortness of breath; sweating; pain

spreading to arms, neck or shoulders; or

lightheadedness • frequent chest pain • frequent

wheezing particularly with heartburn • unexplained

weight loss • nausea or vomiting • stomach pain

Stop use and ask a doctor if • your

heartburn continues or worsens • you

need to take this product for more than

14 days

If pregnant or breast-feeding,

ask a health professional before use.

Keep

out of reach of children. In case of

overdose, get medical help or contact a Poison

Control Center right away.

Inactive ingredients hydroxypropyl

cellulose, hypromellose, iron oxide red, magnesium

stearate, microcrystalline cellulose, polyethylene

glycol 400, pregelatinized starch, talc, titanium

dioxide

PACKAGE LABEL

MM1